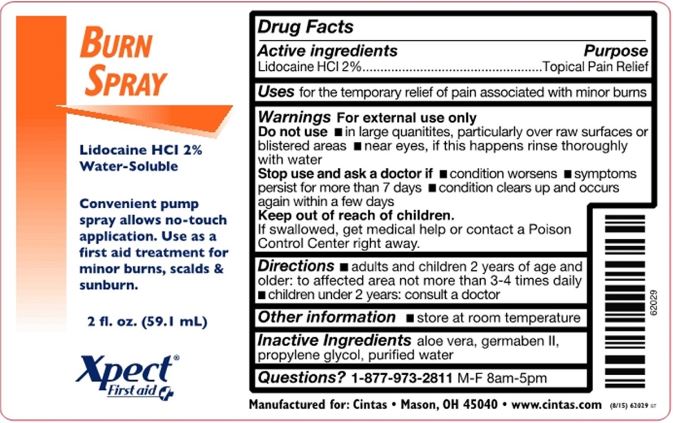 DRUG LABEL: Xpect Burn Care
NDC: 42961-213 | Form: SPRAY
Manufacturer: Cintas Corp
Category: otc | Type: HUMAN OTC DRUG LABEL
Date: 20250923

ACTIVE INGREDIENTS: LIDOCAINE HYDROCHLORIDE 2 mg/100 mL
INACTIVE INGREDIENTS: ALOE VERA WHOLE; DIAZOLIDINYL UREA; PROPYLENE GLYCOL; WATER

Xpect Burn Care

Active Ingredients

Lidocaine HCl 2%

Purpose

Topical Pain Relief

Uses

For the temporary relief of pain associated with minor burns

Warnings

For external use only

Do not use

- in large quanitites, particularly over raw surfaces or blistered areas
- near eyes, if this happens rinse thoroughly with water

Stop use and ask a doctor if

- condition worsens
- symptoms persist for more than 7 days
- condition clears up and occurs again within a few days

Keep out of reach of children.

If swallowed, get medical help or contact a Poison Control Center right away.

Directions

- adults and children 2 years of age and older: to affected area not more than 3-4 times daily
- children under 2 years: consult a doctor

Other information

- store at room temperature

Inactive Ingredients

aloe vera, germaben II, propylene glycol, purified water

Questions?

1-877-973-2811 M-F 8am-5pm

Principal Display Panel

Burn Spray

Lidocaine HCl 2%

Water-Soluble

Convenient pump spray allows no-touch application. Use as a first aid treatment for minor burns, scalds & sunburn.

2 fl. oz. (59.1 mL)

Xpect® First aid

Manufactured for: Cintas • Mason, OH 45040 www.cintas.com